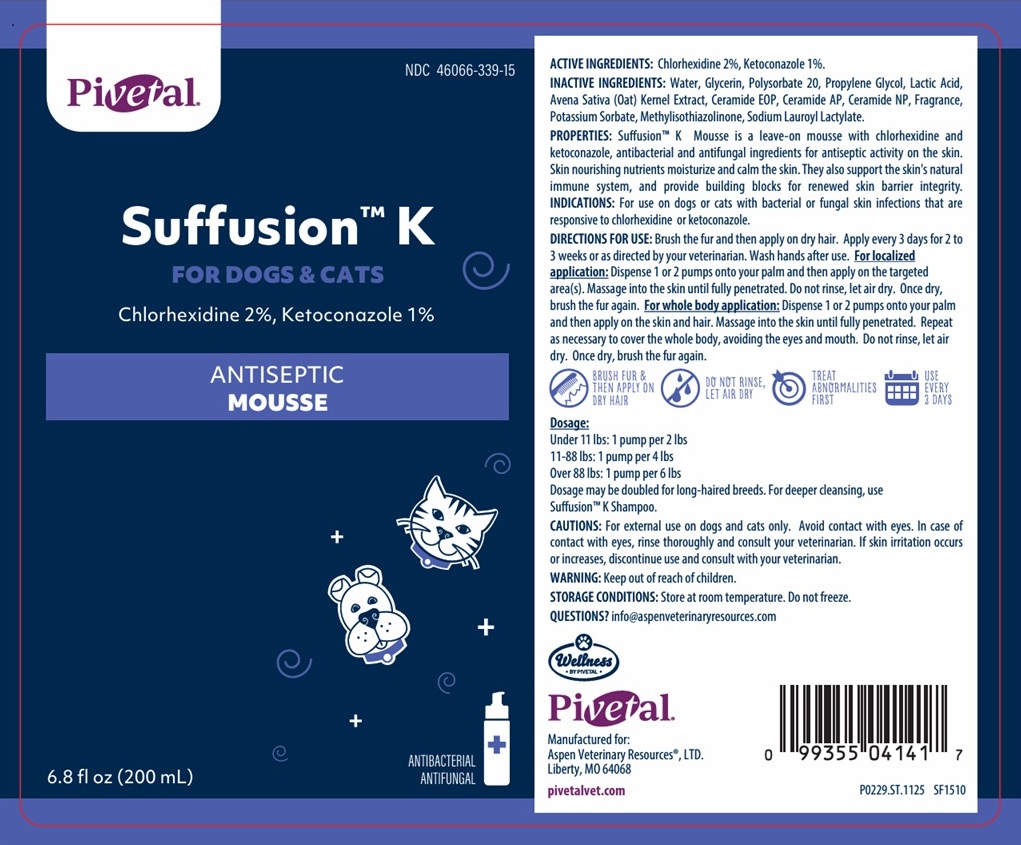 DRUG LABEL: Suffusion K ANTISEPTIC MOUSSE
NDC: 46066-339 | Form: AEROSOL, FOAM
Manufacturer: Aspen Veterinary Resources, LTD.
Category: animal | Type: OTC ANIMAL DRUG LABEL
Date: 20260212

ACTIVE INGREDIENTS: CHLORHEXIDINE 2 g/100 mL; KETOCONAZOLE 1 g/100 mL
INACTIVE INGREDIENTS: WATER; GLYCERIN; POLYSORBATE 20; PROPYLENE GLYCOL; LACTIC ACID, UNSPECIFIED FORM; OAT; CERAMIDE 9; CERAMIDE AP; CERAMIDE NP; POTASSIUM SORBATE; METHYLISOTHIAZOLINONE; SODIUM LAUROYL LACTYLATE

Pivetal® Suffusion™ K ANTISEPTIC MOUSSE

ACTIVE INGREDIENTS:

Chlorhexidine 2%, Ketoconazole 1%.

INACTIVE INGREDIENTS:

Water, Glycerin, Polysorbate 20, Propylene Glycol, Lactic Acid, Avena Sativa (Oat) Kernel Extract, Ceramide EOP, Ceramide AP, Ceramide NP, Fragrance, Potassium Sorbate, Methylisothiazolinone, Sodium Lauroyl Lactylate.

PROPERTIES:

Suffusion™ K Mousse is a leave-on mousse with chlorhexidine and ketoconazole, antibacterial and antifungal ingredients for antiseptic activity on the skin. Skin nourishing nutrients moisturize and calm the skin. They also support the skin's natural immune system, and provide building blocks for renewed skin barrier integrity.

INDICATIONS:

For use on dogs or cats with bacterial or fungal skin infections that are responsive to chlorhexidine or ketoconazole.

DIRECTIONS FOR USE:

Brush the fur and then apply on dry hair. Apply every 3 days for 2 to 3 weeks or as directed by your veterinarian. Wash hands after use. For localized application: Dispense 1 or 2 pumps onto your palm and then apply on the targeted area(s). Massage into the skin until fully penetrated. Do not rinse, let air dry. Once dry, brush the fur again. For whole body application: Dispense 1 or 2 pumps onto your palm and then apply on the skin and hair. Massage into the skin until fully penetrated. Repeat as necessary to cover the whole body, avoiding the eyes and mouth. Do not rinse, let air dry. Once dry, brush the fur again.

BRUSH FUR & THEN APPLY ON DRY HAIR

DO NOT RINSE, LET AIR DRY

TREAT ABNORMALITIES FIRST

USE EVERY 3 DAYS

Dosage:
Under 11 lbs: 1 pump per 2 lbs
11-88 lbs: 1 pump per 4 lbs
Over 88 lbs: 1 pump per 6 lbs
Dosage may be doubled for long-haired breeds. For deeper cleaning, use Suffusion™ K Shampoo.

CAUTIONS:

For external use on dogs and cats only. Avoid contact with eyes. In case of contact with eyes, rinse thoroughly and consult your veterinarian. If skin irritation occurs or increases, discontinue use and consult with your veterinarian.

WARNING:

Keep out of reach of children.

STORAGE CONDITIONS:

Store at room temperature. Do not freeze.

QUESTIONS?

info@aspenveterinaryresources.com

FOR DOGS & CATS

ANTIBACTERIAL
ANTIFUNGAL

Manufactured for:
Aspen Veterinary Resources® , LTD.
Liberty, MO 64068

pivetalvet.com